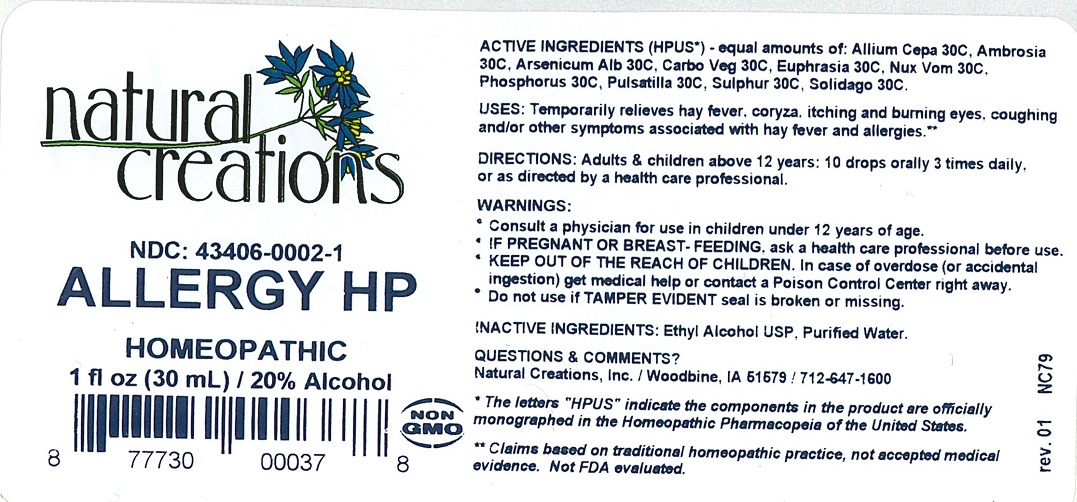 DRUG LABEL: Allergy HP
NDC: 43406-0002 | Form: LIQUID
Manufacturer: Natural Creations, Inc.
Category: homeopathic | Type: HUMAN OTC DRUG LABEL
Date: 20220217

ACTIVE INGREDIENTS: ONION 30 [hp_C]/1 mL; AMBROSIA ARTEMISIIFOLIA 30 [hp_C]/1 mL; ARSENIC TRIOXIDE 30 [hp_C]/1 mL; ACTIVATED CHARCOAL 30 [hp_C]/1 mL; EUPHRASIA STRICTA 30 [hp_C]/1 mL; STRYCHNOS NUX-VOMICA SEED 30 [hp_C]/1 mL; PULSATILLA VULGARIS 30 [hp_C]/1 mL; SOLIDAGO VIRGAUREA FLOWERING TOP 30 [hp_C]/1 mL; SULFUR 30 [hp_C]/1 mL
INACTIVE INGREDIENTS: WATER; ALCOHOL

Allergy HP

ACTIVE INGREDIENT

Active Ingredients (HPUS*): Allium Cepa 30C, Ambrosia Artemisiifolia 30C, Arsenicum Album 30C, Carbo Vegetabilis 30C, Euphrasia Officinalis 30C, Nux Vomica 30C, Phosphorus 30C, Pulsatilla 30C, Solidago Virgaurea 30C, Sulfur 30C

INDICATIONS AND USAGE

USES: Temporarily relieves hay fever, coryza, itching & burning eyes, coughing &/or other symptoms associated with hay fever & allergies.**

WARNING:

- Consult a physician for use in children under 12 years of age.
- IF PREGNANT OR BREAST-FEEDING, ask a health professional before use.
- KEEP OUT OF THE REACH OF CHILDREN. In case of overdose (or accidental ingestion) get medical help or contact a Poison Control Center right away.
- Do not use if TAMPER EVIDENT seal is broken or missing.

DOSAGE AND ADMINISTRATION

DIRECTIONS: Adults and children above 12 years: 10 drops orally 3 times daily, or as directed by a heath care professional.

REFERENCES

*The letters "HPUS" indicate the components in the product are officially monographed in the Homeopathic Pharmacopeia of the United States.

**Claims based on traditional homeopathic practice, not accepted medical evidence. Not FDA evaluated.

INACTIVE INGREDIENTS: Ethyl Alcohol USP, Purified Water.

QUESTIONS AND COMMENTS?

Natural Creations, Inc. / Woodbine, IA 51579 / 712-647-1600

PURPOSE

USES: Temporarily relieves hay fever, coryza, itching & burning eyes, coughing &/or other symptoms associated with hay fever & allergies.**

KEEP OUT OF REACH OF CHILDREN

KEEP OUT OF THE REACH OF CHILDREN. In case of overdose (or accidental ingestion) get medical help or contact a Poison Control Center right away.

PACKAGE LABEL

NDC: 43406-0002-1

ALLERGY HP

HOMEOPATHIC

1 fl oz (30 mL) / 20% Alcohol

UPC: 87730000378